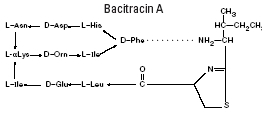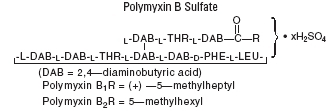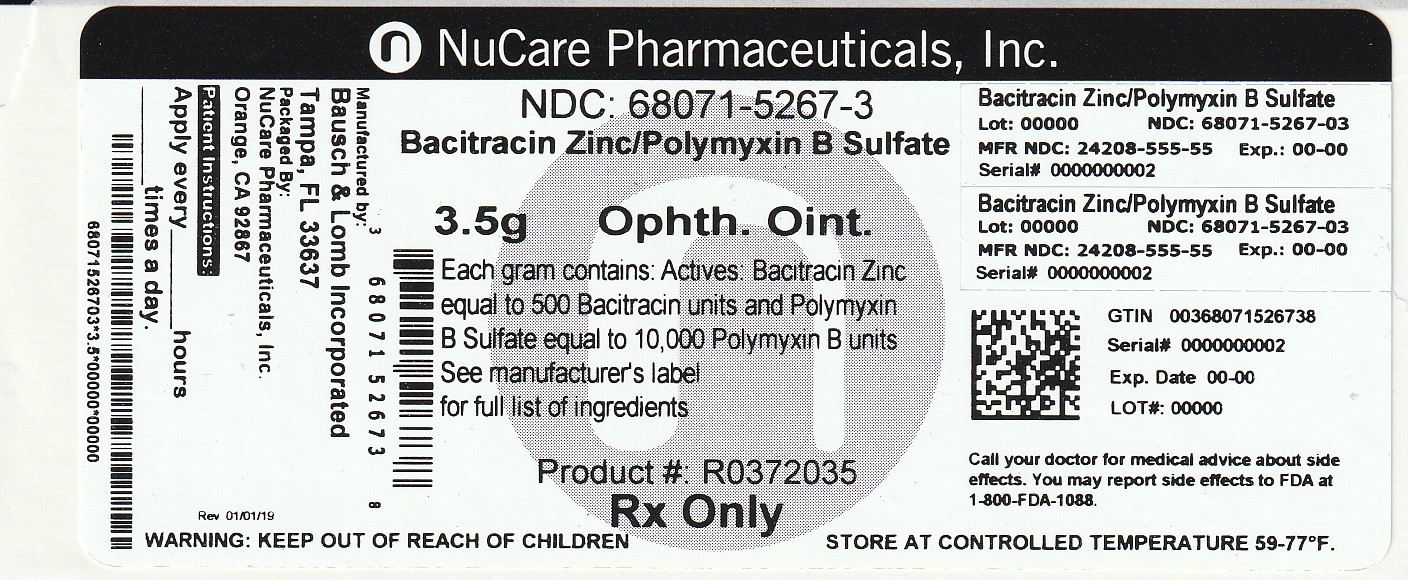 DRUG LABEL: Bacitracin Zinc and Polymyxin B Sulfate
NDC: 68071-5267 | Form: OINTMENT
Manufacturer: NuCare Pharmaceuticals,Inc.
Category: prescription | Type: HUMAN PRESCRIPTION DRUG LABEL
Date: 20241230

ACTIVE INGREDIENTS: BACITRACIN ZINC 500 [USP'U]/1 g; POLYMYXIN B SULFATE 10000 [USP'U]/1 g
INACTIVE INGREDIENTS: MINERAL OIL; PETROLATUM

Bacitracin Zinc and Polymyxin B Sulfate Ophthalmic Ointment, USP (Sterile)

Rx only

DESCRIPTION

Bacitracin Zinc and Polymyxin B Sulfate Ophthalmic Ointment, USP is a sterile antimicrobial ointment formulated for ophthalmic use.

Bacitracin zinc is the zinc salt of bacitracin, a mixture of related cyclic polypeptides (mainly bacitracin A) produced by the growth of an organism of the licheniformis group of Bacillus subtilis var Tracy. It has a potency of not less than 40 bacitracin units/mg. The structural formula for bacitracin A is:

Polymyxin B sulfate is the sulfate salt of polymyxin B1 and B2, which are produced by the growth of Bacillus polymyxa (Prazmowski) Migula (Fam. Bacillaceae). It has a potency of not less than 6,000 polymyxin B units/mg, calculated on an anhydrous basis. The structural formulae are:

Each gram contains: Actives: Bacitracin Zinc equal to 500 bacitracin units and Polymyxin B Sulfate equal to 10,000 polymyxin B units; Inactives: Mineral Oil and White Petrolatum.

CLINICAL PHARMACOLOGY

Polymyxin B sulfate attacks gram-negative bacilli, including virtually all strains of Pseudomonas aeruginosa and Haemophilus influenzae species.

Bacitracin is active against most gram-positive bacilli and cocci including hemolytic streptococci.

INDlCATlONS AND USAGE

For the treatment of superficial ocular infections involving the conjunctiva and/or cornea caused by organisms susceptible to bacitracin zinc and polymyxin B sulfate.

CONTRAINDICATIONS

This product is contraindicated in those individuals who have shown hypersensitivity to any of its components.

WARNINGS

Ophthalmic ointments may retard corneal healing.

PRECAUTIONS

As with other antibiotic preparations, prolonged use may result in overgrowth of nonsusceptible organisms, including fungi. Appropriate measures should be taken if this occurs.

ADVERSE REACTIONS

To report SUSPECTED ADVERSE REACTIONS, contact Bausch & Lomb Incorporated at 1-800-321-4576 or FDA at 1-800-FDA-1088 or www.fda.gov/medwatch.

DOSAGE AND ADMINISTRATION

Apply the ointment every 3 or 4 hours for 7 to 10 days, depending on the severity of the infection.

FOR OPHTHALMIC USE ONLY

HOW SUPPLIED

Bacitracin Zinc and Polymyxin B Sulfate Ophthalmic Ointment, USP is available in tubes with an ophthalmic tip applicator in the following size:

tube of 3.5g -NDC 68071-5267-3

Storage

Store between 15° to 25°C (59° to 77°F). KEEP TIGHTLY CLOSED

Keep out of reach of children.

Distributed by:

Bausch + Lomb, a division of Bausch Health US, LLC

Bridgewater, NJ 08807 USA

Manufactured by:

Bausch & Lomb Incorporated

Tampa, FL 33637 USA

© 2020 Bausch & Lomb Incorporated or its affiliates

Revised: February 2020

9130703 (Folded)

9130603 (Flat)